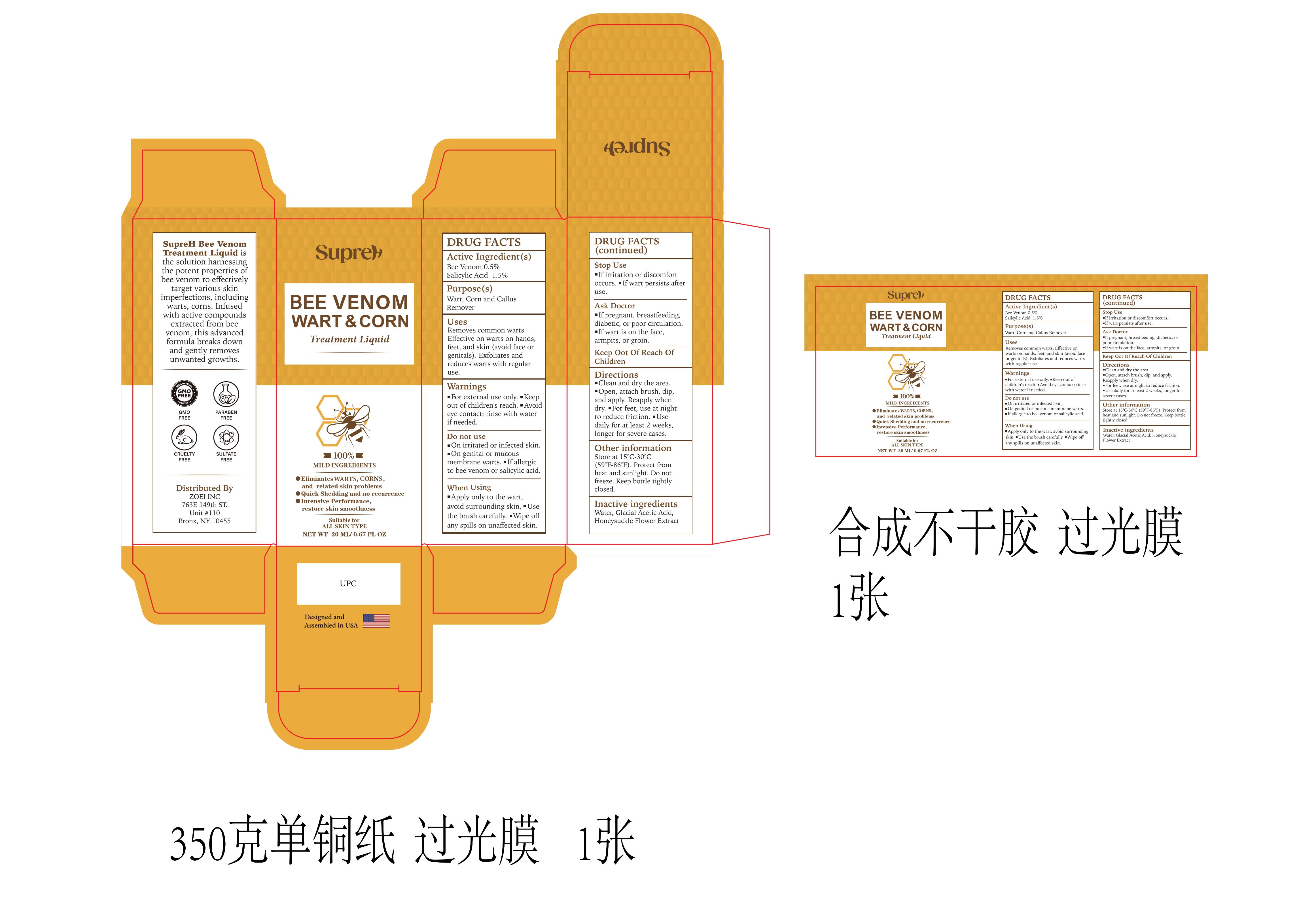 DRUG LABEL: SupreH Bee Venom Wart  Corn Treatment
NDC: 83818-005 | Form: LIQUID
Manufacturer: Shenzhen Xinxin Yunhai Technology Co., Ltd.
Category: otc | Type: HUMAN OTC DRUG LABEL
Date: 20241024

ACTIVE INGREDIENTS: APIS MELLIFERA VENOM 0.5 g/100 mL; SALICYLIC ACID 1.5 g/100 mL
INACTIVE INGREDIENTS: LONICERA CAPRIFOLIUM (HONEYSUCKLE) FLOWER EXTRACT; ACETIC ACID

83818-005

Active Ingredient

Bee Venom 0.5%
Salicylic Acid 1.5%

Purpose

wart, corn and callus remover

Use

Removes common warts.
Effective on warts on hands, feet, and skin (avoid face or genitals).
Exfoliates and reduces warts with regular use.

Warnings

For external use only.
Keep out of children's reach.
Avoid eye contact; rinse with water if needed.

Do not use

On irritated or infected skin.
On genital or mucous membrane warts.
If allergic to bee venom or salicylic acid.

When Using

Apply only to the wart, avoid surrounding skin.
Use the brush carefully.
Wipe off any spills on unaffected skin.

Stop Use

If irritation or discomfort occurs.
If wart persists after use.

Ask Doctor

If pregnant, breastfeeding, diabetic, or poor circulation.
If wart is on the face, armpits, or groin.

Keep Oot Of Reach Of Children

Please keep the product out of reach of children. If accidentally ingested, please call the emergency center immediately.

Directions

1.Clean and dry the area.
2.Open, attach brush, dip, and apply. Reapply when dry.
3.For feet, use at night to reduce friction.
4.Use daily for at least 2 weeks, longer for severe cases.

Other information

Store at 15°C-30°C (59°F-86°F). Protect from heat and sunlight. Do not freeze.
Keep bottle tightly closed.

Inactive ingredients

Water, Glacial Acetic Acid, Honeysuckle Flower Extract